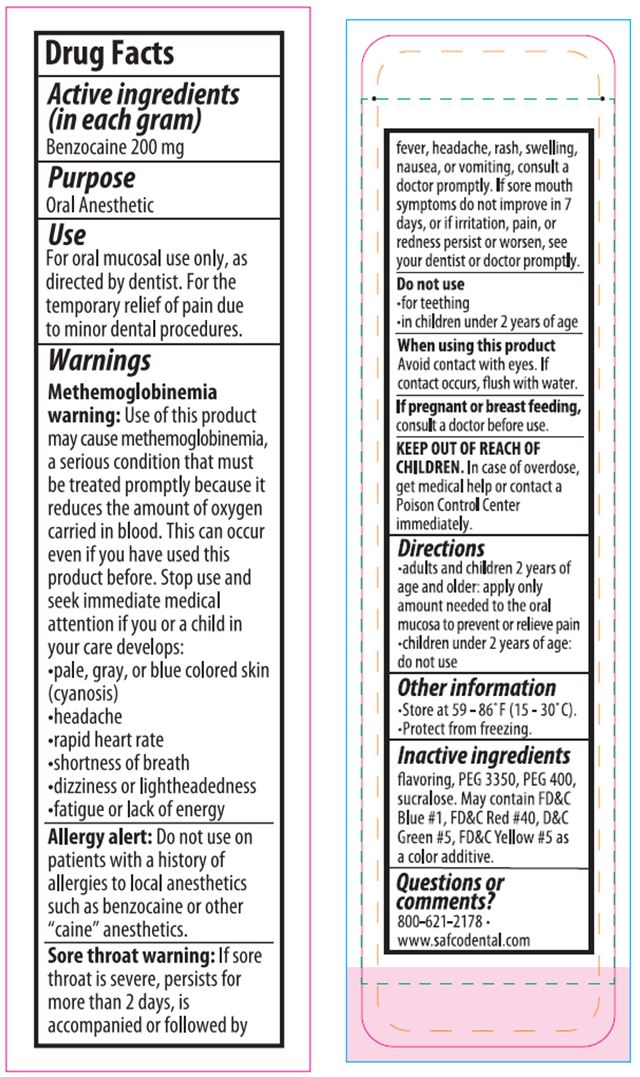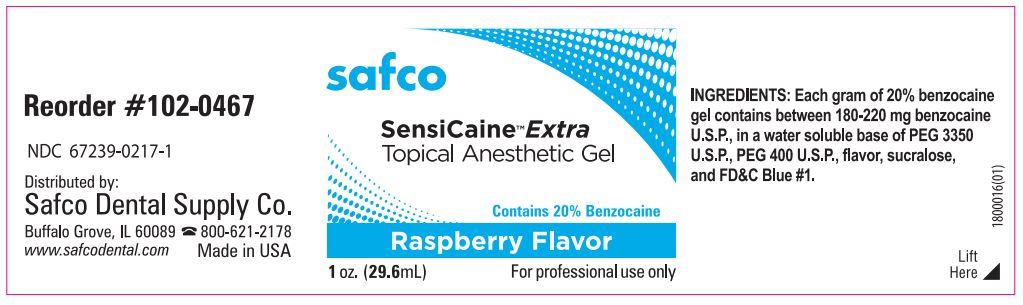 DRUG LABEL: Sensicaine TM Extra
NDC: 67239-0217 | Form: GEL
Manufacturer: Safco Dental Supply Co.
Category: otc | Type: HUMAN OTC DRUG LABEL
Date: 20181111

ACTIVE INGREDIENTS: Benzocaine 200 mg/1 g
INACTIVE INGREDIENTS: Polyethylene Glycol 3350; Polyethylene Glycol 400; Sucralose; FD&C BLUE NO. 1

SensiCaineTM Extra Topical Anesthetic Gel Raspberry Flavor

Active ingridients (in each gram)

Benzocaine 200 mg

Purpose

Oral Anesthetic

Use

For oral mucosal use only, as directed by dentist. For the temporary relief of pain due to minor dental procedures.

Warnings

Methemoglobinemia warning: Use of this product may cause methemoglobinemia, a serious condition that must be treated promptly because it reduces the amount of oxygen carried in blood.This can occur even if you have used this product before. Stop use and seek immediate medical attention if you or a child in your care develops:

- pale, gray, or blue colored skin (cyanosis)
- headache
- rapid heart rate
- shortness of breath
- dizziness or lightheadedness
- fatigue or lack of energy

Allergy alert: Do not use on patients with a history of allergies to local anesthetics such as benzocaine or other "caine" anesthetics.

Sore throat warning:If sore throat is severe,persists for more than 2 days,is accompanied or followed by fever, headache, rash, swelling, nausea,or vomiting, consult a doctor promptly.If sore mouth symptoms do not improve in 7 days, or if irritation,pain, or redness persist or worsen, see your dentist or doctor promptly.

Do not use

- for teething
- in children under 2 years of age

When using this product Avoid contact with eyes. If contact occurs, flush with water.

PREGNANCY OR BREAST FEEDING

If pregnant or breast feeding, consult a doctor before use.

KEEP OUT OF REACH OF CHILDREN. In case of overdose, get medical help or contact a Poison Control Center immediately.

Directions

- adults and children 2 years of age and older: apply only amount needed to the oral mucosa to prevent or relieve pain
- children under 2 years of age: do not use

Other information

- Store at 59 - 86ºF (15 - 30ºC).
- Protect from freezing.

Inactive ingredients

flavoring, PEG 3350, PEG 400, sucralose and FD&C Blue #1, FD&C Red #40, D&C Green #5, FD&C Yellow #5 as a color additive.

Questions or comments?

800-621-2178

www.safcodental.com

PRINCIPAL DISPLAY PANEL - Jar Label

SAFCO
SensiCaineTM Extra

Topical Anesthetic Gel

Contains 20% Benzocaine

Raspberry Flavor

For Professional Use Only

1 oz. (34 g)